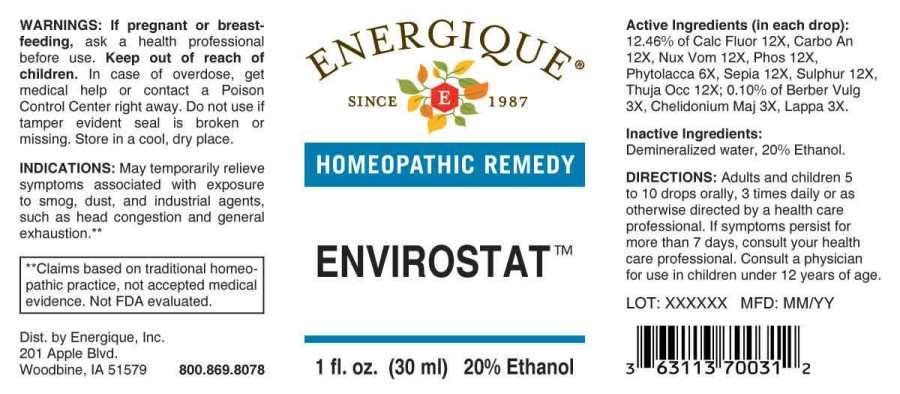 DRUG LABEL: Envirostat
NDC: 44911-0483 | Form: LIQUID
Manufacturer: Energique, Inc.
Category: homeopathic | Type: HUMAN OTC DRUG LABEL
Date: 20231004

ACTIVE INGREDIENTS: BERBERIS VULGARIS ROOT BARK 3 [hp_X]/1 mL; CHELIDONIUM MAJUS WHOLE 3 [hp_X]/1 mL; ARCTIUM LAPPA ROOT 3 [hp_X]/1 mL; PHYTOLACCA AMERICANA ROOT 6 [hp_X]/1 mL; CALCIUM FLUORIDE 12 [hp_X]/1 mL; CARBO ANIMALIS 12 [hp_X]/1 mL; STRYCHNOS NUX-VOMICA SEED 12 [hp_X]/1 mL; PHOSPHORUS 12 [hp_X]/1 mL; SEPIA OFFICINALIS JUICE 12 [hp_X]/1 mL; SULFUR 12 [hp_X]/1 mL; THUJA OCCIDENTALIS LEAF 12 [hp_X]/1 mL
INACTIVE INGREDIENTS: WATER; ALCOHOL

DRUG FACTS:

ACTIVE INGREDIENTS:

(in each drop): 12.46% of Calcarea Fluorica 12X, Carbo Animalis 12X, Nux Vomica 12X, Phosphorus 12X, Phytolacca Decandra 6X, Sepia 12X, Sulphur 12X, Thuja Occidentalis 12X; 0.10% of Berberis Vulgaris 3X, Chelidonium Majus 3X, Lappa Major 3X.

INDICATIONS:

May temporarily relieve symptoms associated with exposure to smog, dust, and industrial agents, such as head congestion and general exhaustion.**

**Claims based on traditional homeopathic practice, not accepted medical evidence. Not FDA evaluated.

WARNINGS:

If pregnant or breast-feeding, ask a health professional before use.

Keep out of reach of children. In case of overdose, get medical help or contact a Poison Control Center right away.

Do not use if tamper evident seal is broken or missing. Store in a cool, dry place.

KEEP OUT OF REACH OF CHILDREN:

In case of overdose, get medical help or contact a Poison Control Center right away.

DIRECTIONS:

Adults and children 5 to 10 drops orally, 3 times daily or as otherwise directed by a health care professional. If symptoms persist for more than 7 days, consult your health care professional. Consult a physician for use in children under 12 years of age.

INDICATIONS:

May temporarily relieve symptoms associated with exposure to smog, dust, and industrial agents, such as head congestion and general exhaustion.**

**Claims based on traditional homeopathic practice, not accepted medical evidence. Not FDA evaluated.

INACTIVE INGREDIENTS:

Demineralized water, 20% Ethanol.

QUESTIONS:

Dist. by Energique, Inc.

201 Apple Blvd

Woodbine, IA 51579 800.869.8078

PACKAGE LABEL DISPLAY:

ENERGIQUE

SINCE 1987

HOMEOPATHIC REMEDY

ENVIROSTAT

1 fl. oz. (30 ml)